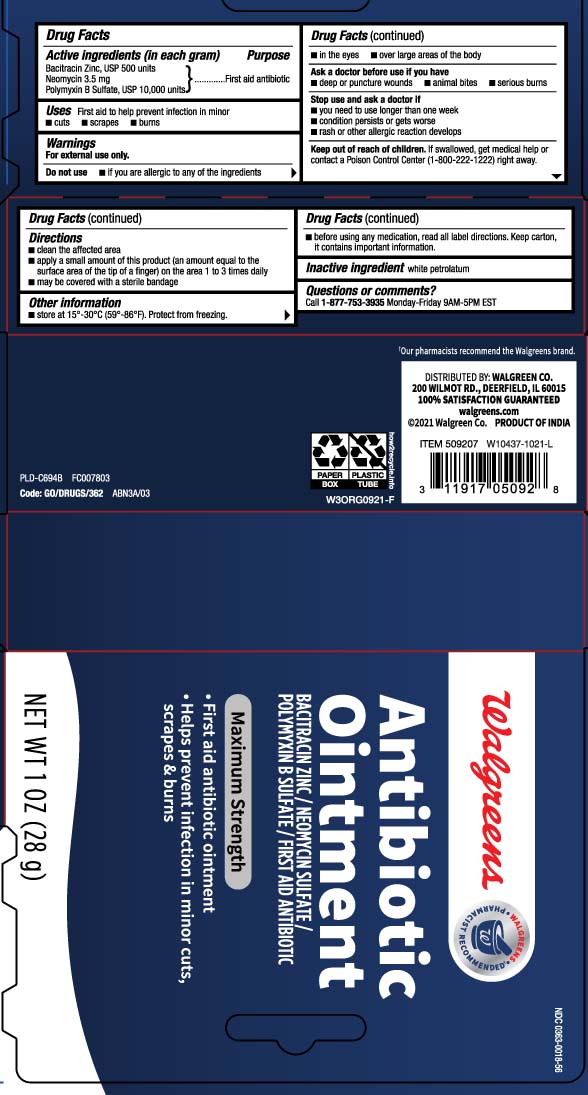 DRUG LABEL: Antibiotic
NDC: 0363-0018 | Form: OINTMENT
Manufacturer: Walgreens
Category: otc | Type: HUMAN OTC DRUG LABEL
Date: 20250902

ACTIVE INGREDIENTS: BACITRACIN ZINC 500 [iU]/1 g; NEOMYCIN SULFATE 3.5 mg/1 g; POLYMYXIN B SULFATE 10000 [iU]/1 g
INACTIVE INGREDIENTS: PETROLATUM

Antibiotic Ointment (Bacitracin Zinc, Neomycin Sulfate, Polymyxin B Sulfate)

Active ingredients (in each gram)

Bacitracin zinc, USP 500 units
Neomycin 3.5 mg
Polymyxin B sulfate, USP 10,000 units

Purpose

First aid antibiotic

Uses

First aid to help prevent infection in minor

- cuts
- scrapes
- burns

Warnings

For external use only

Do not use

- if you are allergic to any of the ingredients
- in the eyes
- over large areas of the body

Ask a doctor before use if you have

- deep or puncture wounds
- animal bites
- serious burns

Stop use and ask a doctor if

- you need to use longer than one week
- condition persists or gets worse
- a rash or other allergic reaction develops

Keep out of reach of children.

If swallowed, get medical help or contact a Poison Control Center (1-800-222-1222) right away.

Directions

- clean affected area
- apply a small amount of this product (an amount equal to the surface area of the tip of a finger) on the area 1 to 3 times daily
- may be covered with a sterile bandage

Other information

- Store at 15º-30ºC (59º-86ºF) Protect from freezing.
- Before using any medication, read all label directions. Keep carton, it contains important information.

Inactive ingredient

white petrolatum

Questions or comments?

Call 1-877-753-3935 Monday-Friday 9AM-5PM EST

Principal display panel

Antibiotic Ointment

BACITRACIN ZINC /

NEOMYCIN SULFATE /

POLYMYXIN B SULFATE

MAXIMUM STRENGTH

- First aid antibiotic ointment
- Help prevent infection in minor cuts, scrapes & burns

NET WT OZ (g)

DISTRIBUTED BY: WALGREEN CO.

200 WILMOT RD., DEERFIELD, IL 60015

Package label

WALGREENS Antibiotic Ointment